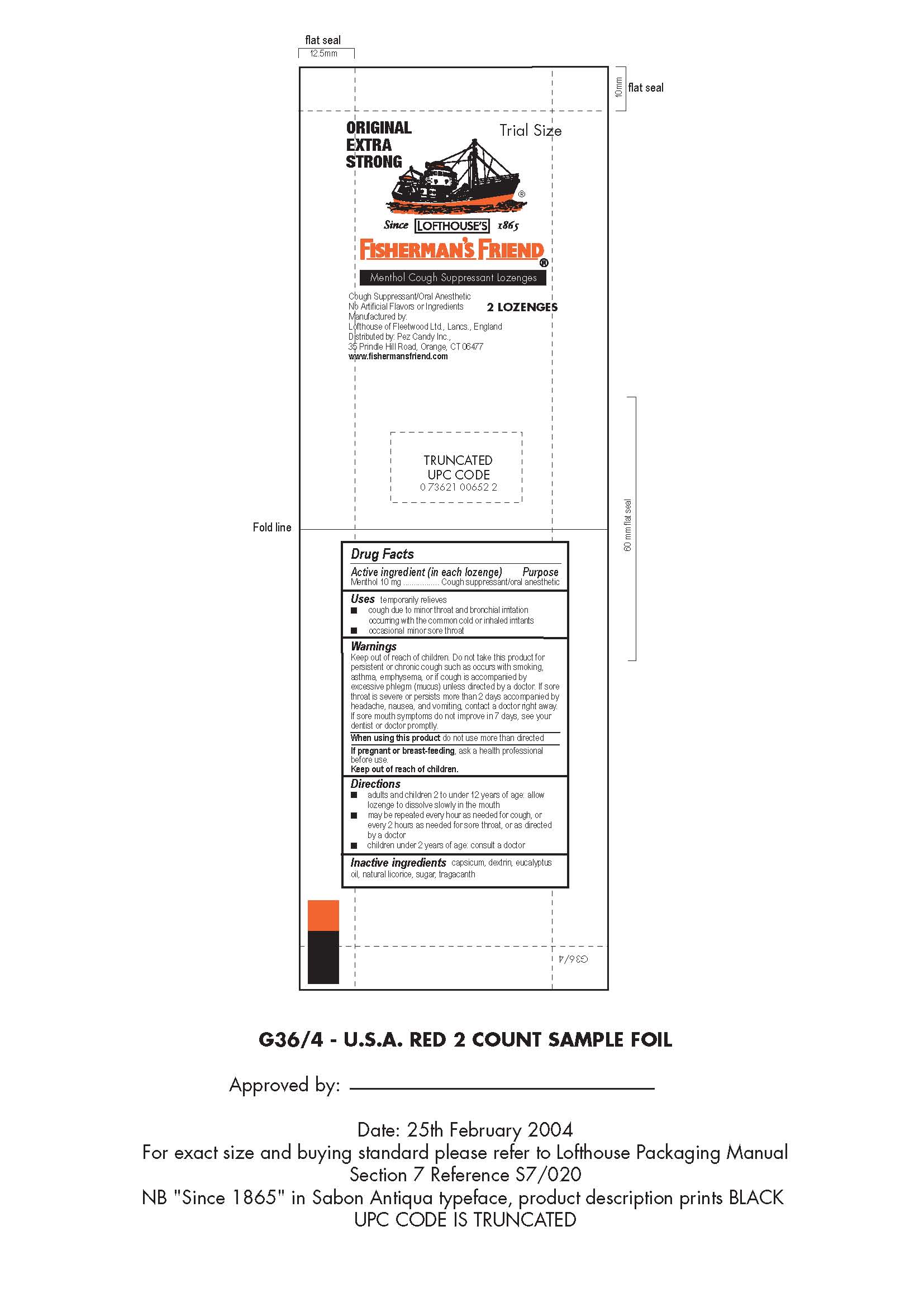 DRUG LABEL: Original Extra Strong All Natural Fishermans Friend Menthol Cough Suppressant
NDC: 55711-064 | Form: LOZENGE
Manufacturer: Lofthouse of Fleetwood, Ltd.
Category: otc | Type: HUMAN OTC DRUG LABEL
Date: 20210625

ACTIVE INGREDIENTS: MENTHOL 10 mg/1 1
INACTIVE INGREDIENTS: CAPSICUM; EUCALYPTUS OIL; LICORICE; RAW SUGAR; TRAGACANTH

064-05

Active ingredient (in each lozenge)

Menthol 10 mg

Purpose

Cough suppressant/oral anesthetic

Uses

temporarily relieves

- cough due to minor throat and bronchial irritation occurring with the common cold or inhaled irritants
- occasional minor sore throat

Warnings

Do not take this product for persistent or chronic cough such as occurs with smoking, asthma, emphysema, or if cough is accompanied by excessive phlegm (mucus) unless directed by a doctor. If sore throat is severe or persists more than 2 days accompanied by headache, nausea, and vomiting, contact a doctor right away. If sore mouth symptoms do not improve in 7 days, see your dentist of doctor promptly.

Keep out of reach of children.

When using this product do not use more than directed

PREGNANCY OR BREAST FEEDING

If pregnant or breast-feeding, ask a health professional before use

Directions

- adults and children 2 to under 12 years of age: allow lozenge to dissolve slowly in the mouth
- may be repeated every hour as needed for cough, or every 2 hours as needed for sore throat, or as directed by a doctor
- children under 2 years of age: consult a doctor

Inactive ingredients

capsicum, dextrin, eucalyptus oil, natural licorice, sugar, tragacanth

Principal Display Panel

Original

Extra

Strong

Trial Size

Since Lofthouse's 1865

Fisherman's Friend

Menthol Cough Suppressant Lozenges

Cough Suppressant/Oral Anesthetic

No Artificial Flavors or Ingredients

2 Lozenges

Manufactured by:

Lofthouse of Fleetwood Ltd., Lancs., England

Distributed by: Pez Candy Inc.

35 Prindle Hill Road, Orange, CT 06477

www.fishermansfriend.com